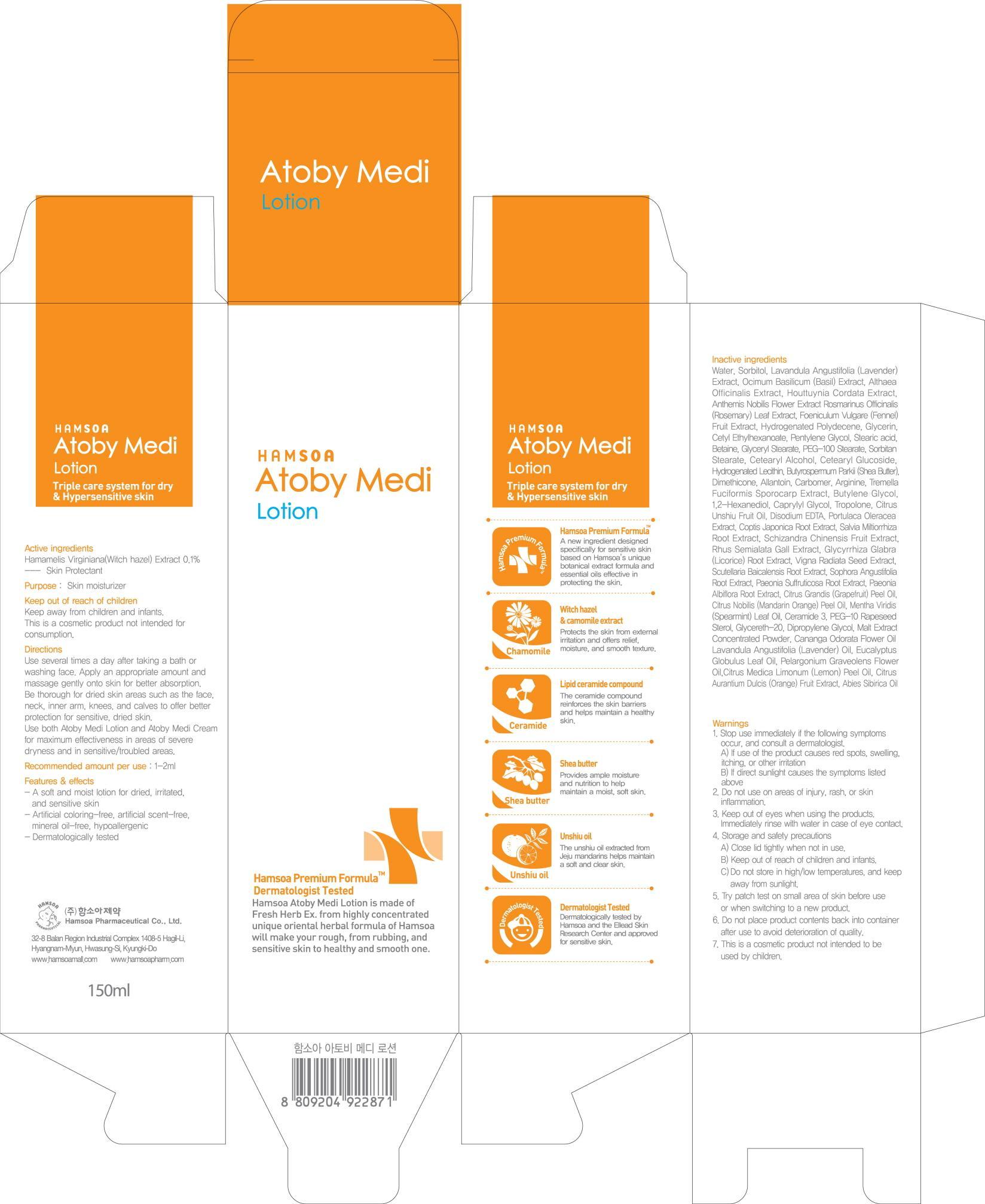 DRUG LABEL: HAMSOA ATOBY MEDI
NDC: 50964-040 | Form: LOTION
Manufacturer: HAMSOA PHARMACEUTICAL CO., LTD.
Category: otc | Type: HUMAN OTC DRUG LABEL
Date: 20120820

ACTIVE INGREDIENTS: WITCH HAZEL 0.15 g/150 mL
INACTIVE INGREDIENTS: WATER; SORBITOL; LAVENDER OIL; BASIL; GLYCERIN; CETYL ETHYLHEXANOATE

Active ingredient

Active ingredient: Witch hazel(Hamamelis Virginiana) 0.1%

Inactive ingredient

Inactive ingredients:
Water, Sorbitol, Lavandula Angustifolia (Lavender) Extract, Ocimum Basilicum (Basil) Extract, Althaea Officinalis Extract, Houttuynia Cordata Extract, Anthemis Nobilis Flower Extract, Rosmarinus Officinalis (Rosemary) Leaf Extract, Foeniculum Vulgare (Fennel) Fruit Extract, Hydrogenated Polydecene, Glycerin, Cetyl Ethylhexanoate, Pentylene Glycol, Stearic acid, Betaine, Glyceryl Stearate, PEG-100 Stearate, Sorbitan Stearate, Cetearyl Alcohol, Cetearyl Glucoside, Hydrogenated Lecithin, Butyrospermum Parkii (Shea Butter), Dimethicone, Allantoin, Carbomer, Arginine, Tremella Fuciformis Sporocarp Extract, Butylene Glycol, 1,2-Hexanediol, Caprylyl Glycol, Tropolone, Citrus Unshiu Fruit Oil, Disodium EDTA, Portulaca Oleracea Extract, Coptis Japonica Root Extract, Salvia Miltiorrhiza Root Extract, Schizandra Chinensis Fruit Extract, Rhus Semialata Gall Extract, Glycyrrhiza Glabra (Licorice) Root Extract, Vigna Radiata Seed Extract, Scutellaria Baicalensis Root Extract, Sophora Angustifolia Root Extract, Paeonia Suffruticosa Root Extract, Paeonia Albiflora Root Extract, Citrus Grandis (Grapefruit) Peel Oil, Citrus Nobilis (Mandarin Orange) Peel Oil, Mentha Viridis (Spearmint) Leaf Oil, Ceramide 3, PEG-10 Rapeseed Sterol, Glycereth-20, Dipropylene Glycol, Malt Extract Concentrated Powder, Cananga Odorata Flower Oil, Lavandula Angustifolia (Lavender) Oil,
Eucalyptus Globulus Leaf Oil, Pelargonium Graveolens Flower Oil, Citrus Medica Limonum (Lemon) Peel Oil, Citrus Aurantium Dulcis (Orange) Fruit Extract, Abies Sibirica Oil

Purpose

Purpose: Skin moisturizer

Warnings

1. Stop use immediately if the following symptoms occur, and consult a dermatologist.
A) If use of the product causes red spots, swelling, itching, or other irritation
B) If direct sunlight causes the symptoms listed above
2. Do not use on areas of injury, rash, or skin inflammation.
3. Keep out of eyes when using the products. Immediately rinse with water in case of eye contact.
4. Storage and safety precautions
A) Close lid tightly when not in use.
B) Keep out of reach of children and infants.
C)Do not store in high/low temperatures, and keep away from sunlight.
5. Try patch test on small area of skin before use or when switching to a new product.
6. Do not place product contents back into container after use to avoid deterioration of quality.
7. This is a cosmetic product not intended to be used by children.

Keep out of reach of children

Keep away from children and infants.
This is a cosmetic product not intended for consumption.

DOSAGE AND ADMINISTRATION

Recommended amount per use: 1-2g

INDICATIONS AND USAGE

Use several times a day after taking a bath or washing face.
Apply an appropriate amount and massage gently onto skin for better absorption.
Be thorough for dried skin areas such as the face, neck, inner arm, knees, and calves to offer better protection for sensitive, dried skin.
Use both Atoby Medi Lotion and Atoby Medi Cream for maximum effectiveness in areas of severe dryness and in sensitive/troubled areas.